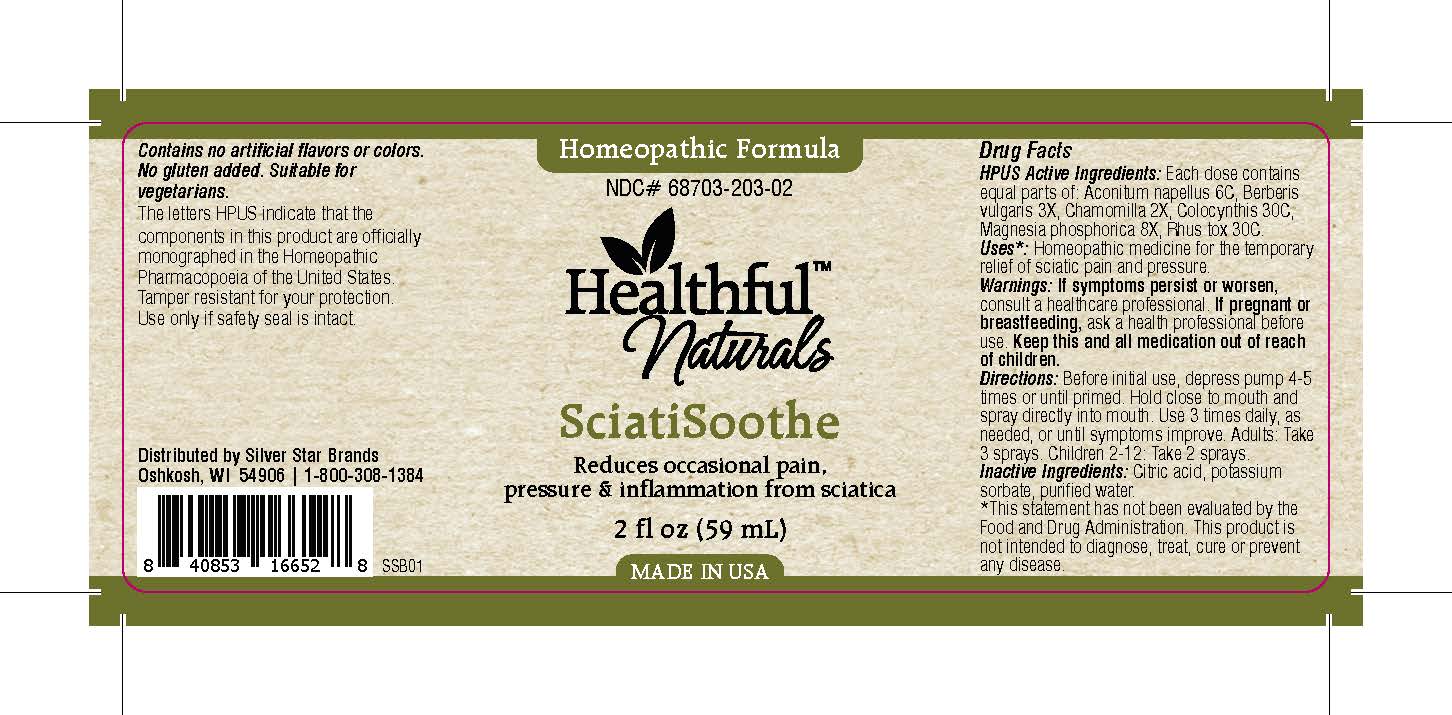 DRUG LABEL: SciatiSoothe
NDC: 68703-203 | Form: SPRAY
Manufacturer: Silver Star Brands
Category: homeopathic | Type: HUMAN OTC DRUG LABEL
Date: 20151020

ACTIVE INGREDIENTS: MAGNESIUM PHOSPHATE, DIBASIC TRIHYDRATE 8 [hp_X]/59 mL; TOXICODENDRON PUBESCENS LEAF 30 [hp_C]/59 mL; MATRICARIA RECUTITA 2 [hp_X]/59 mL; ACONITUM NAPELLUS 6 [hp_C]/59 mL; BERBERIS VULGARIS ROOT BARK 3 [hp_X]/59 mL; CITRULLUS COLOCYNTHIS FRUIT PULP 30 [hp_C]/59 mL
INACTIVE INGREDIENTS: POTASSIUM SORBATE; ANHYDROUS CITRIC ACID; WATER

Healthful™ Naturals SciatiSoothe

HPUS Active Ingredients

Each dose contains equal parts of: Aconitum napellus 6C, Berberis vulgaris 3X, Chamomilla 2X, Colocynthis 30C, Magnesia phosphorica 8X, Rhus tox 30C.

Uses

*Homeopathic medicine for the temporary relief of sciatic pain and pressure. *This statement has not been evaluated by the Food and Drug Administration. This product is not intended to diagnose, treat, cure or prevent any disease.

Warnings

If symptoms persist or worsen, consult a healthcare professional. If pregnant or breastfeeding, ask a health professional before use. Keep this and all medication out of reach of children.

Directions

Before initial use, depress pump 4-5 times or until primed. Hold close to mouth and spray directly into mouth. Use 3 times daily, as needed, or until symptoms improve. Adults: Take 3 sprays. Children 2-12: Take 2 sprays.

Other Information

Contains no artificial flavors or colors. No gluten added. Suitable for vegetarians. The letters HPUS indicate that the components in this product are officially monographed in the Homeopathic Pharmacopoeia of the United States. Tamper resistant for your protection. Use only if safety seal is intact.

INACTIVE INGREDIENT

Citric acid, potassium sorbate, purified water.

KEEP OUT OF REACH OF CHILDREN

Keep this and all medication out of reach of children.

PREGNANCY OR BREAST FEEDING

If pregnant or breastfeeding, ask a health professional before use.

PURPOSE

Reduces occasional pain, pressure & inflammation from sciatica